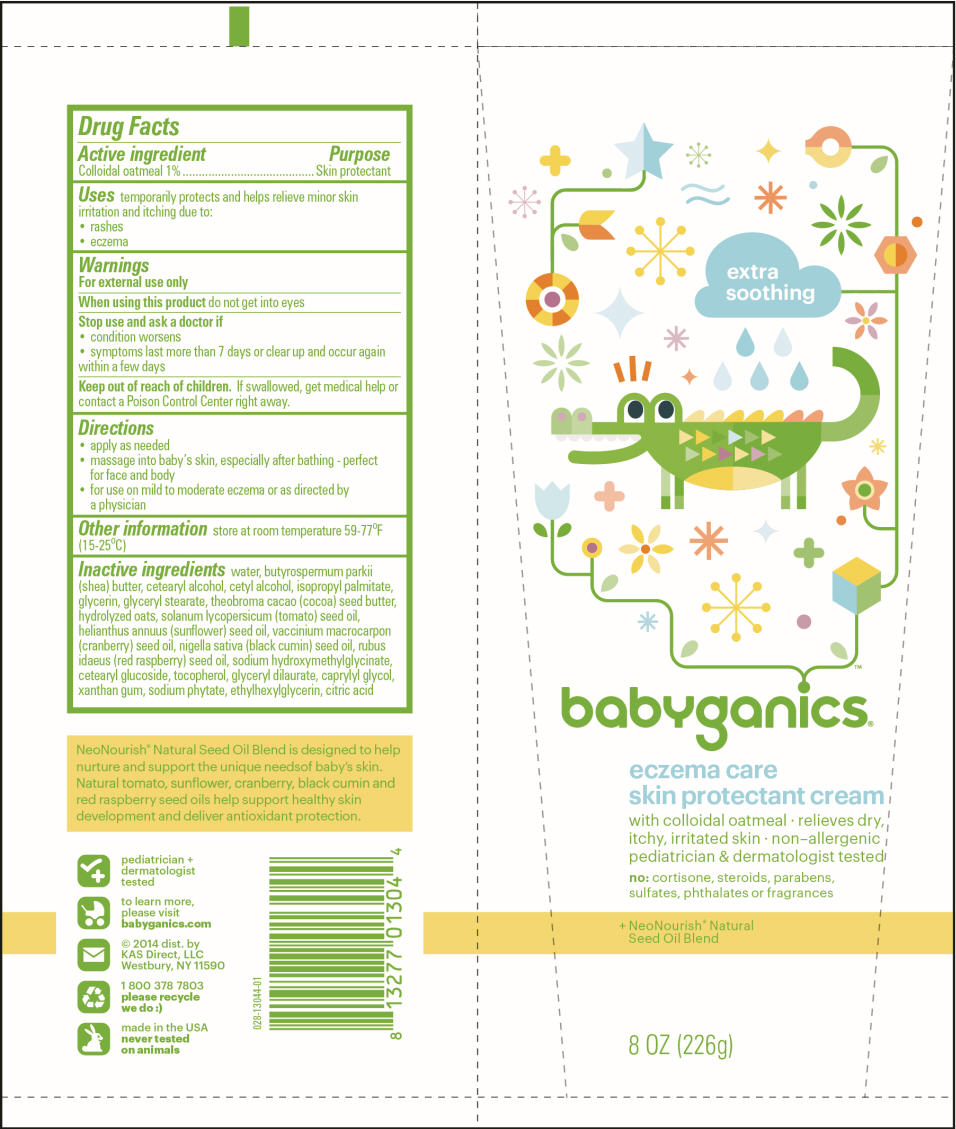 DRUG LABEL: BABYGANICS ECZEMA
NDC: 59062-1304 | Form: LOTION
Manufacturer: KAS Direct LLC dba BabyGanics
Category: otc | Type: HUMAN OTC DRUG LABEL
Date: 20180122

ACTIVE INGREDIENTS: OATMEAL 10 mg/1 g
INACTIVE INGREDIENTS: WATER; SHEA BUTTER; CETOSTEARYL ALCOHOL; CETYL ALCOHOL; ISOPROPYL PALMITATE; GLYCERIN; GLYCERYL MONOSTEARATE; COCOA BUTTER; OAT; NIGELLA SATIVA SEED OIL; CARROT SEED OIL; CHIA SEED OIL; RASPBERRY SEED OIL; CRANBERRY SEED OIL; CETEARYL GLUCOSIDE; TOCOPHEROL; GLYCERYL DILAURATE; CAPRYLYL GLYCOL; XANTHAN GUM; PHYTATE SODIUM; ETHYLHEXYLGLYCERIN; CITRIC ACID MONOHYDRATE; SODIUM HYDROXYMETHYLGLYCINATE

babyganics® Eczema Lotion

Drug Facts

Active ingredient

Colloidal oatmeal 1%

Purpose

Skin protectant

Uses

temporarily protects and helps relieve minor skin irritation and itching due to:

- rashes
- eczema

Warnings

For external use only

When using this product do not get into eyes

Stop use and ask a doctor if

- condition worsens
- symptoms last more than 7 days or clear up and occur again within a few days

Keep out of reach of children. If swallowed, get medical help or contact a Poison Control Center right away.

Directions

- apply as needed
- massage into baby's skin, especially after bathing - perfect for face and body
- for use on mild to moderate eczema or as directed by a physician

Other information

Store at room temperature 59-77°F (15-25°C)

Inactive ingredients

water, butyrospermum parkii (shea) butter, cetearyl alcohol, cetyl alcohol, isopropyl palmitate, glycerin, glyceryl stearate, theobroma cacao (cocoa) seed butter, hydrolyzed oats, solanum lycopersicum (tomato) seed oil, helianthus annuus (sunflower) seed oil, vaccinium macrocarpon (cranberry) seed oil, nigella sativa (black cumin) seed oil, rubus idaeus (red raspberry) seed oil, cetearyl glucoside, tocopherol, glyceryl dilaurate, caprylyl glycol, xanthan gum, sodium phytate, ethylhexylglycerin, citric acid, sodium hydroxymethylglycinate

Dist. by:
KAS Direct, LLC.
Hicksville, NY 11801

PRINCIPAL DISPLAY PANEL - 226 g Tube Label

extra
soothing

babyganics®

eczema care
skin protectant cream

with colloidal oatmeal ∙ relieves dry,
itchy, irritated skin ∙ non–allergenic
pediatrician & dermatologist tested

no: cortisone, steroids, parabens,
sulfates, phthalates or fragrances

+ NeoNourish® Natural
Seed Oil Blend

8 OZ (226g)